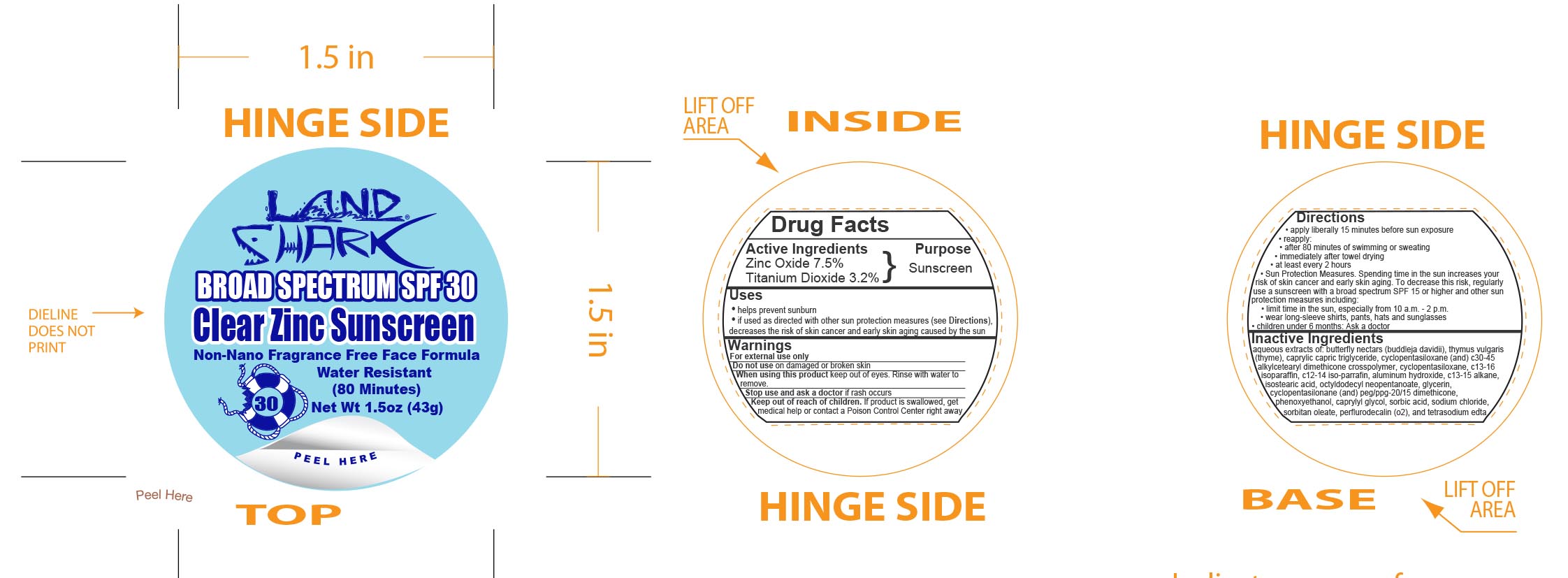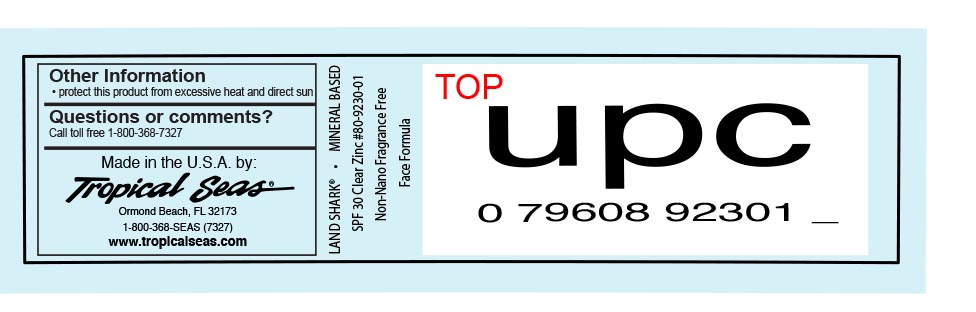 DRUG LABEL: Land Shark SPF 30 Clear Zinc
NDC: 52854-943 | Form: CREAM
Manufacturer: Tropical Seas, Inc.
Category: otc | Type: HUMAN OTC DRUG LABEL
Date: 20251104

ACTIVE INGREDIENTS: ZINC OXIDE 7.5 g/100 g; TITANIUM DIOXIDE 3.2 g/100 g
INACTIVE INGREDIENTS: ALUMINUM HYDROXIDE; WATER; BUDDLEJA DAVIDII LEAF; THYMUS VULGARIS LEAF; CAPRYLIC/CAPRIC ACID; DIMETHICONE CROSSPOLYMER (450000 MPA.S AT 12% IN CYCLOPENTASILOXANE); C13-16 ISOPARAFFIN; C12-14 ISOPARAFFIN; C13-15 ALKANE; ISOSTEARIC ACID; PEG/PPG-20/15 DIMETHICONE; BIS-PHENYLPROPYL DIMETHICONE (15 CST); GLYCERIN; OCTYLDODECYL NEOPENTANOATE; PERFLUOROMETHYLDECALIN; PHENOXYETHANOL; CAPRYLYL GLYCOL; SORBIC ACID; SODIUM CHLORIDE; SORBITAN MONOOLEATE; DITETRACYCLINE TETRASODIUM EDETATE

Land Shark SPF 30 Clear Zinc

Drug Facts

Active Ingredients

Zinc Oxide 7.5%

Titanium Dioxide 3.2%

Purpose

Sunscreen

Uses

- helps prevent sunburn
- if used as directed with other sun protection measures (see Directions), decreases the risk of skin cancer and early skin aging caused by the sun

Warnings

For external use only

Do not use on damaged or broken skin

When using this product keep out of eyes. Rinse with water to remove.

Stop use and ask a doctor if rash occurs

Keep out of reach of children. If product is swallowed, get medical help or contact a Poison Control Center right away.

Directions

- apply liberally 15 minutes before sun exposure
- reapply:
  - after 80 minutes of swimming or sweating
  - immediately after towel drying
  - at least every 2 hours
- Sun Protection Measures. Spending time in the sun increases your risk of skin cancer and early skin aging. To decrease this risk, regularly use a sunscreen with a broad spectrum SPF 15 or higher and other sun protection measures including:
  - limit time in the sun, especially from 10 a.m. - 2 p.m.
  - wear long-sleeve shirts, pants, hats and sunglasses
- children under 6 months: Ask a doctor

Inactive Ingredients

aqueous extracts of: butterfly nectars (buddleja davidii), thymus vulgaris (thyme), caprylic capric triglyceride, cyclopentasiloxane (and) c30-45 alkylcetearyl dimethicone crosspolymer, c13-16 isoparaffin, c12-14 iso-parrafin, aluminum hydroxide, c13-15 alkane, isostearic acid, octyldodecyl neopentanoate, glycerin, cyclopentasilonane (and) peg/ppg-20/15 dimethicone, phenoxyethanol, caprylyl glycol, sorbic acid, sodium chloride, sorbitan leate, perflurodecalin (o2), and tetrasodium edta.

Other Information

- protect this product from excessive heat and direct sun

Questions or comments?

Call toll free 1-800-368-7327

Principal Display Panel - 43 g Jar Label

43g NDC 52854-930-03